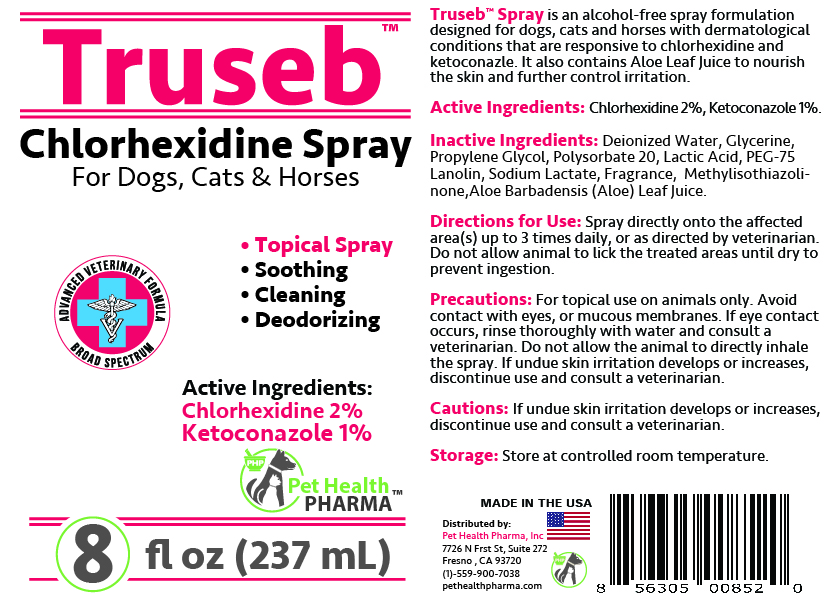 DRUG LABEL: Truseb Chlorhexidine Gluconate, Ketoconazole For Cats, Dogs and Horses
NDC: 86176-203 | Form: SPRAY
Manufacturer: Pet Health Pharma, LLC
Category: animal | Type: OTC ANIMAL DRUG LABEL
Date: 20250210

ACTIVE INGREDIENTS: CHLORHEXIDINE GLUCONATE 2 g/100 mL; KETOCONAZOLE 1 g/100 mL
INACTIVE INGREDIENTS: WATER; GLYCERIN; PROPYLENE GLYCOL; Polysorbate 20; Lactic Acid; PEG-75 Lanolin; Sodium Lactate; Methylisothiazolinone; ALOE VERA LEAF

Truseb™ Topical Chlorhexidine Gluconate, Ketoconazole Spray For Cats, Dogs & Horses

Active Ingredients:

Chlorhexidine Gluconate 2% and Ketoconazole 1%

INDICATIONS & USAGE:

Truseb™ Spray is an alcohol-free spray formulation designed for dogs, cats and horses. It also contains Aloe Vera leaf juice to nourish the skin and further control irritation.

INACTIVE INGREDIENTS:

Deionized Water, Glycerine, Propylene Glycol, Polysorbate 20, Lactic Acid, PEG-75 Lanolin, Sodium Lactate, Fragrance, Methylisothiazolinone, Aloe Barbadensis (Aloe) Leaf Juice.

PRECAUTIONS:

For topical use on animals only. Avoid contact with eyes, or mucous membranes. If eye contact occurs, rinse thoroughly with water and consult a veterinarian. Do not allow the animal to directly inhale the spray. If undue skin irritation develops or increases, discontinue use and consult a veterinarian.

CAUTIONS:

If undue skin irritation develops or increases, discontinue use and consult a veterinarian.

DIRECTIONS FOR USE:

Spray directly onto the affected area(s) up to 3 times daily, or as directed by veterinarian. Do not allow animal to lick the treated areas until dry to prevent ingestion.

STORAGE:

Store at controlled room temperature.

SPL UNCLASSIFIED SECTION

Chlorhexidine Spray
For Dogs, Cats & Horses

ADVANCED VETERINARY FORMULA
Broad Spectrum

• Topical Spray
• Soothing
• Cleaning
• Deodorizing
MADE IN THE USA

Distributed by:
Pet Health Pharma, Inc
7726 N Frst St, Suite 272
Fresno , CA 93720
(1)-559-900-7038
pethealthpharma.com

PRINCIPAL DISPLAY PANEL

PHP008-OL

Add image transcription here...